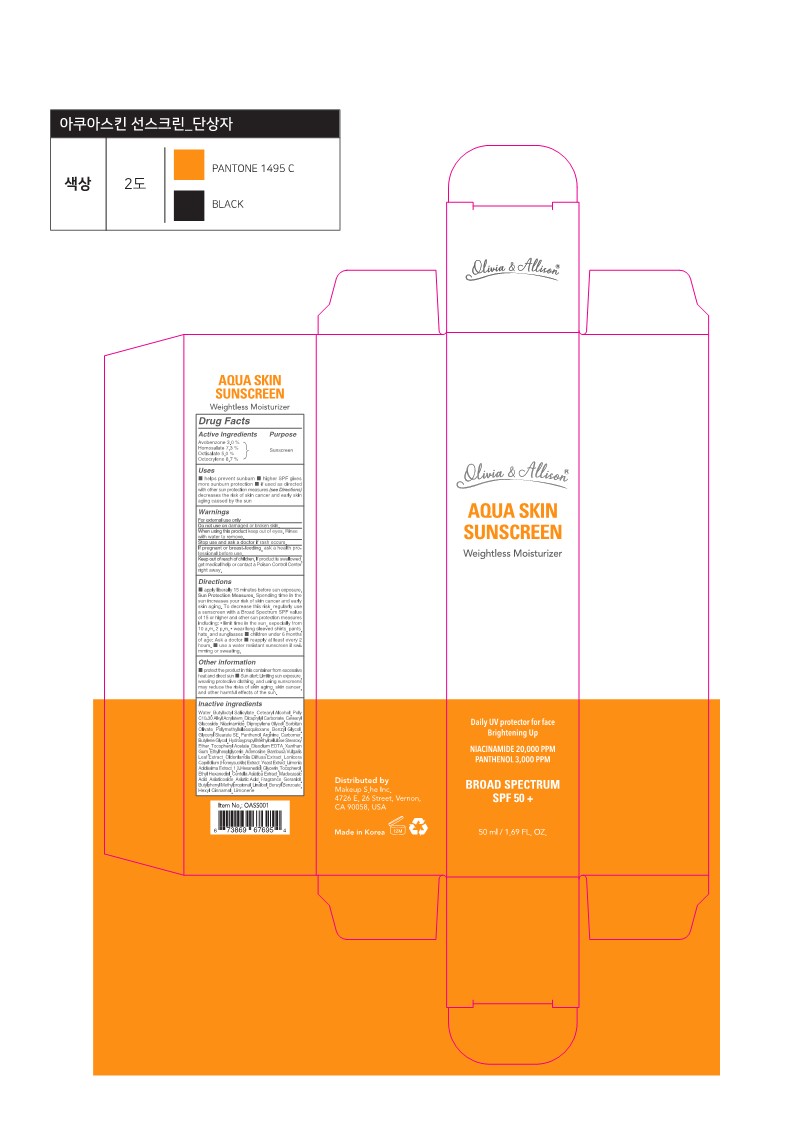 DRUG LABEL: Olivia and Allison AQUA SKIN SUNSCREEN
NDC: 84122-050 | Form: CREAM
Manufacturer: Makeup S.he, Inc.
Category: otc | Type: HUMAN OTC DRUG LABEL
Date: 20240215

ACTIVE INGREDIENTS: OCTISALATE 2.5 g/50 mL; AVOBENZONE 1.5 g/50 mL; OCTOCRYLENE 4.35 g/50 mL; HOMOSALATE 3.65 g/50 mL
INACTIVE INGREDIENTS: DICAPRYLYL CARBONATE; ETHYLENE GLYCOL MONOBENZYL ETHER; 1,2-HEXANEDIOL; ASIATICOSIDE; BUTYLPHENYL METHYLPROPIONAL; BENZYL BENZOATE; GLYCERYL STEARATE SE; ETHOHEXADIOL; .ALPHA.-TOCOPHEROL ACETATE; CENTELLA ASIATICA TRITERPENOIDS; LIMONENE, (+)-; .ALPHA.-HEXYLCINNAMALDEHYDE; CARBOMER HOMOPOLYMER, UNSPECIFIED TYPE; EDETATE DISODIUM ANHYDROUS; XANTHAN GUM; GERANIOL; CETOSTEARYL ALCOHOL; BAMBUSA VULGARIS LEAF; CETEARYL GLUCOSIDE; ASIATIC ACID; WATER; MADECASSIC ACID; SCLEROMITRION DIFFUSUM; BUTYLENE GLYCOL; ETHYLHEXYLGLYCERIN; ADENOSINE; YEAST; GLYCERIN; TOCOPHEROL; BUTYLOCTYL SALICYLATE; NIACINAMIDE; DIPROPYLENE GLYCOL; SORBITAN OLIVATE; POLYMETHYLSILSESQUIOXANE (4.5 MICRONS); PANTHENOL; ARGININE; LINALOOL, (+/-)-

Olivia and Allison AQUA SKIN SUNSCREEN

Active ingredients

Avobenzone 3.0%

Homosalate 7.3%

Octisalate 5.0%

Octocrylene 8.7%

Purpose

sunscreen

Uses

■ helps prevent sunburn ■ higher SPF gives more sunburn protection

■ if used as directed with other sun protection measures (see Directions) decreases the risk of skin cancer and early skin aging caused by the sun

Warnings

For external use only

Do not use on

damaged or broken skin.

When using the product

keep out of eyes. Rinse with water to remove.

Stop use and ask a doctor

if rash occurs.

If pregnant or breast-feeding,

ask a health professional before use.

Keep out of reach of children.

If products is swallowed, get medical help or contact a Poison Control Center right away.

Directions

■ apply liberally 15 minutes before sun exposure. Sun Protection Measures. Spending time in the sun increases your risk of skin cancer and early skin aging. To decrease this risk, regularly use a sunscreen with a Broad Spectrum SPF value of 15 or higher and other sun protection measures including: • limit time in the sun, especially from 10 a.m. - 2 p.m. • wear long-sleeved shirts, pants, hats, and sunglasses ■ children under 6 months of age: Ask a doctor ■ reapply at least every 2 hours. ■ use a water-resistant sunscreen if swimming or sweating.

Other information

■ protect the product in this container from excessive heat and direct sun ■ Sun alert: Limiting sun exposure, wearing protective clothing, and using sunscreens may reduce the risks of skin aging, skin cancer, and other harmful effects of the sun.

Inactive ingredients

Water, Butyloctyl Salicylate, Cetearyl Alcohol, Poly C10-30 Alkyl Acrylate, Dicaprylyl Carbonate, Cetearyl Glucoside, Niacinamide, Dipropylene Glycol, Sorbitan Olivate, Polymethylsilsesquioxane, Benzyl Glycol, Glyceryl Stearate SE, Panthenol, Arginine, Carbomer, Butylene Glycol, Hydroxypropyl Methylcellulose Stearoxy Ether, Tocopheryl Acetate, Disodium EDTA, Xanthan Gum, Ethylhexylglycerin, Adenosine, Bambusa Vulgaris Leaf Extract, Oldenlandia Diffusa Extract, Lonicera Caprifolium (Honeysuckle) Extract, Yeast Extract, Limonia Acidissima Extract, 1,2-Hexanediol, Glycerin, Tocopherol, Ethyl Hexanediol, Centella Asiatica Extract, Madecassic Acid, Asiaticoside, Asiatic Acid, Fragrance, Geraniol, Butylphenyl Methylpropional, Linalool, Benzyl Benzoate, Hexyl Cinnamal, Limonene